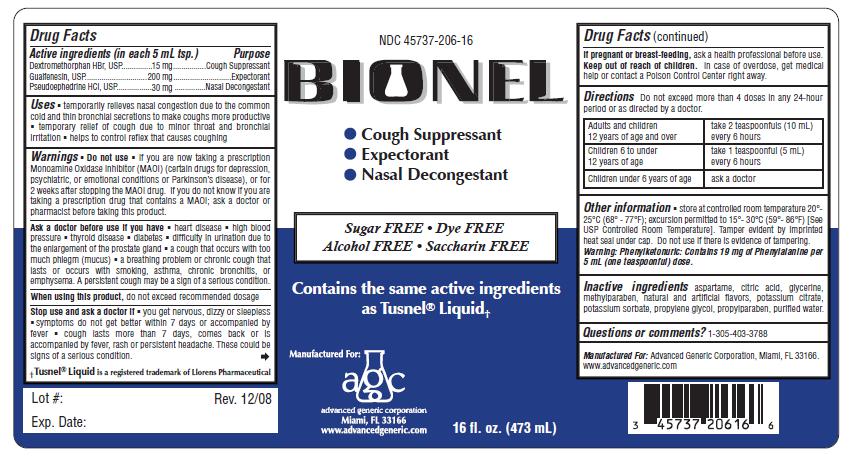 DRUG LABEL: Bionel
NDC: 45737-206 | Form: LIQUID
Manufacturer: Advanced Generic Corporation
Category: otc | Type: HUMAN OTC DRUG LABEL
Date: 20241220

ACTIVE INGREDIENTS: DEXTROMETHORPHAN HYDROBROMIDE 15 mg/5 mL; GUAIFENESIN 200 mg/5 mL; PSEUDOEPHEDRINE HYDROCHLORIDE 30 mg/5 mL
INACTIVE INGREDIENTS: GLYCERIN; WATER; POTASSIUM CITRATE; POTASSIUM SORBATE; PROPYLENE GLYCOL; PROPYLPARABEN; CITRIC ACID MONOHYDRATE; ASPARTAME; METHYLPARABEN

AGC-Bionel 206

Active Ingredients: (in each 5 mL tsp.) Purpose

Guaifenesin 200 mg .............................................. Expectorant
Dextromethorphan Hydrobromide 15 mg.................. Cough Suppressant
Pseudoephedrine HCl 30 mg.................................. Nasal Decongestant

Uses

- temporarily relieves nasal congestion due to the common cold and thin bronchial secretions to make coughs more productive
- temporary relief of cough due to minor throat and bronchial irritation
- helps to control reflex that causes coughing

Warnings
Do not useif you are now taking a prescription
Monoamine Oxidase Inhibitor (MAOI) (certain drugs for depression,
psychiatric, or emotional conditions or Parkinson’s disease), or for
2 weeks after stopping the MAOI drug. If you do not know if you are
taking a prescription drug that contains a MAOI; ask a doctor or
pharmacist before taking this product.

Ask a doctor before use if you hav

e

- heart disease
- high blood pressure
- thyroid disease
- diabetes
- difficulty in urination due to the enlargement of the prostate gland
- a cough that occurs with too much phlegm (mucus)
- a breathing problem or chronic cough that lasts or occurs with smoking, asthma, chronic bronchitis, or emphysema. A persistent cough may be a sign of a serious condition.

Stop use and ask a doctor if

- you get nervous, dizzy or sleepless
- symptoms do not get better within 7 days or accompanied by fever
- cough lasts more than 7 days, comes back or is accompanied by fever, rash or persistent headache. These could be signs of a serious condition.

Keep out of reach of children.

PREGNANCY OR BREAST FEEDING

If pregnant or breast-feeding,ask a health professional before use.

DOSAGE AND ADMINISTRATION

DirectionsDo not exceed 4 doses in 24 hours.
adults and children 12 years of age and over take 2 teaspoonful (10 mL) every 6 hours
children 6 to under 12 years of age take 1 teaspoonful (5 mL) every 4 hours

children under 6 years of age ask a doctor

Other information

store at controlled room temperature 20°- 25°C (68° - 77°F); excursion permitted to 15°- 30°C (59°- 86°F) [See USP Controlled Room Temperature]. Tamper evident by imprinted heat seal under cap. Do not use if there is evidence of tampering.
Warning:Phenylketonuric: Contains 19 mg of Phenylalanine per 5 mL (one teaspoonful) dose.

INACTIVE INGREDIENT

Inactive ingredientsaspartame, citric acid, glycerine, methylparaben, natural and artificial flavors, potassium citrate, potassium sorbate, propylene glycol, propylparaben, purified water

Questions or comments?1-305-403-3788

Manufactured For:Advanced Generic Corporation, Miami, Fl 33166

www.advancedgeneric.com